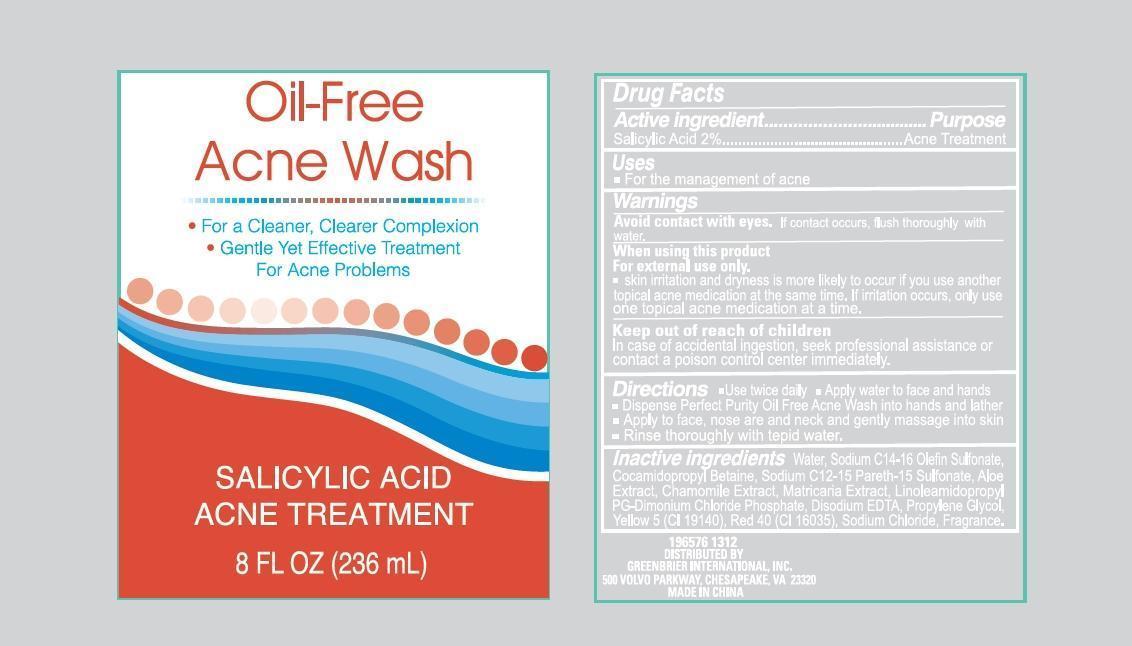 DRUG LABEL: Oil-Free Acne Wash
NDC: 40104-291 | Form: LOTION
Manufacturer: Ningbo Pulisi Daily Chemical Products Co.,Ltd.
Category: otc | Type: HUMAN OTC DRUG LABEL
Date: 20170817

ACTIVE INGREDIENTS: Salicylic acid 20 mg/1 mL
INACTIVE INGREDIENTS: water; SODIUM C14-16 OLEFIN SULFONATE; COCAMIDOPROPYL BETAINE; SODIUM C12-15 PARETH-15 SULFONATE; ALOE VERA LEAF; CHAMAEMELUM NOBILE FLOWER; CHAMOMILE; LINOLEAMIDOPROPYL PG-DIMONIUM CHLORIDE PHOSPHATE; EDETATE DISODIUM; PROPYLENE GLYCOL; FD&C YELLOW NO. 5; FD&C RED NO. 40; SODIUM CHLORIDE

Active ingredients

Salicylic acid ............. 2%

Purpose

Acne Treatment

Use

- Helps fight and prevent acne breakouts on back,shoulders, chest
- For the management of acne

warnings

For external use only.

Avoid contact with eyes, if contact occurs, flush thoroughly with water.

When using this product

- Skin irritation and dryness is more likely to occur if you use another topical acne medication at the same time. If irritation occurs, only use one topical acne medication at a time.

Keep out of reach of children

In case of accidental ingestion, seek professional assistance or contact a Poison Control Center immediately.

Directions

- use as often as needed in shower or bath.
- Apply to washcloth or brush
- Work lather into skin, especially affected areas, rinse well.

Inactive ingredients

water, sodium C14-16 olefin sulfonate, cocamidopropyl betaine, disodium cocoamphodiacetate, sodium C12-15 pareth-15 sulfonate, aloe barbadensis leaf extract, anthemis nobilis flower extract, matricaria (chamomilla recutita) flower extract, linoleamidopropyl PG-dimonium chloride phosphate, disodium EDTA, propylene glycol, yellow 5, red 40 , sodium chloride, fragrance

Principal Display Panel

Acne Body Wash

- Salicylic Acid Acne Treatment
- For a cleaner, Clearer Skin
- Gentle yet effective treatment for acne problems.